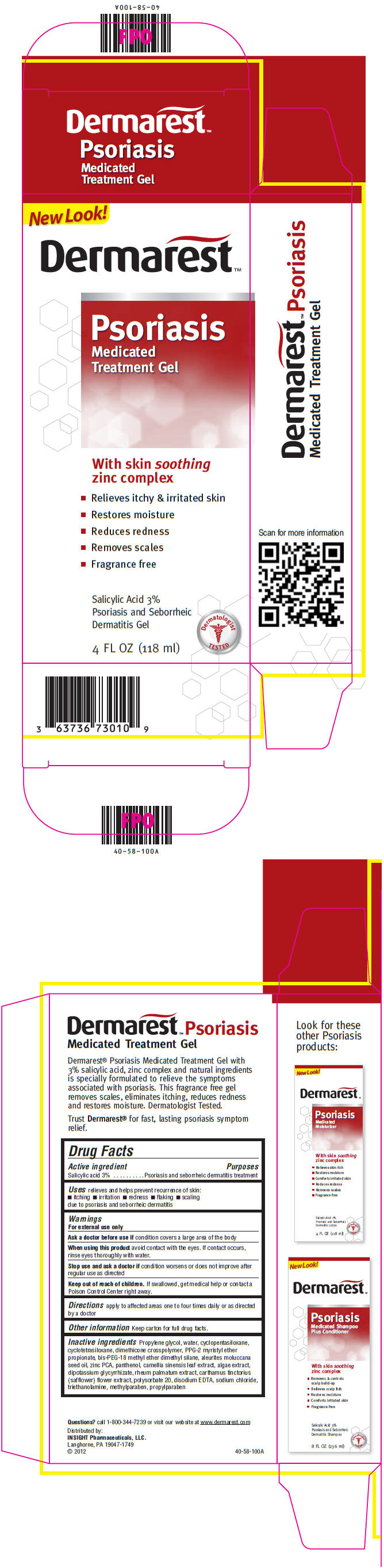 DRUG LABEL: Dermarest 
NDC: 63736-301 | Form: GEL
Manufacturer: Insight Pharmaceuticals
Category: otc | Type: HUMAN OTC DRUG LABEL
Date: 20120404

ACTIVE INGREDIENTS: Salicylic Acid 3.54 mL/118 mL
INACTIVE INGREDIENTS: Propylene Glycol; Water; Cyclomethicone 5; Dimethicone; Ether; Dimethyl Ether; Panthenol; Green Tea Leaf; Safflower; Polysorbate 20; Edetate Disodium; Sodium Chloride; Methylparaben; Propylparaben

Dermarest™
Psoriasis
Medicated
Treatment Gel

Drug Facts

Active ingredient

Salicylic acid 3%

Purposes

Psoriasis and seborrheic dermatitis treatment

Uses

relieves and helps prevent recurrence of skin:

- itching
- irritation
- redness
- flaking
- scaling

due to psoriasis and seborrheic dermatitis

Warnings

For external use only

Ask a doctor before use if condition covers a large area of the body

When using this product avoid contact with the eyes. If contact occurs, rinse eyes thoroughly with water.

Stop use and ask a doctor if condition worsens or does not improve after regular use as directed

Keep out of reach of children. If swallowed, get medical help or contact a Poison Control Center right away.

Directions

apply to affected areas one to four times daily or as directed by a doctor

Other information

Keep carton for full drug facts.

Inactive ingredients

Propylene glycol, water, cyclopentasiloxane, cyclotetrasiloxane, dimethicone crosspolymer, PPG-2 myristyl ether propionate, bis-PEG-18 methyl ether dimethyl silane, aleurites moluccana seed oil, zinc PCA, panthenol, camellia sinensis leaf extract, algae extract, dipotassium glycyrrhizate, rheum palmatum extract, carthamus tinctorius (safflower) flower extract, polysorbate 20, disodium EDTA, sodium chloride, triethanolamine, methylparaben, propylparaben

Questions?

call 1-800-344-7239 or visit our website at www.dermarest.com

Distributed by:
INSIGHT Pharmaceuticals, LLC.
Langhorne, PA 19047-1749

PRINCIPAL DISPLAY PANEL - 118 ml Bottle Carton

New Look!

Dermarest™

Psoriasis
Medicated
Treatment Gel

With skin soothing
zinc complex

- Relieves itchy & irritated skin
- Restores moisture
- Reduces redness
- Removes scales
- Fragrance free

Salicylic Acid 3%
Psoriasis and Seborrheic
Dermatitis Gel

Dermatologist
TESTED

4 FL OZ (118 ml)